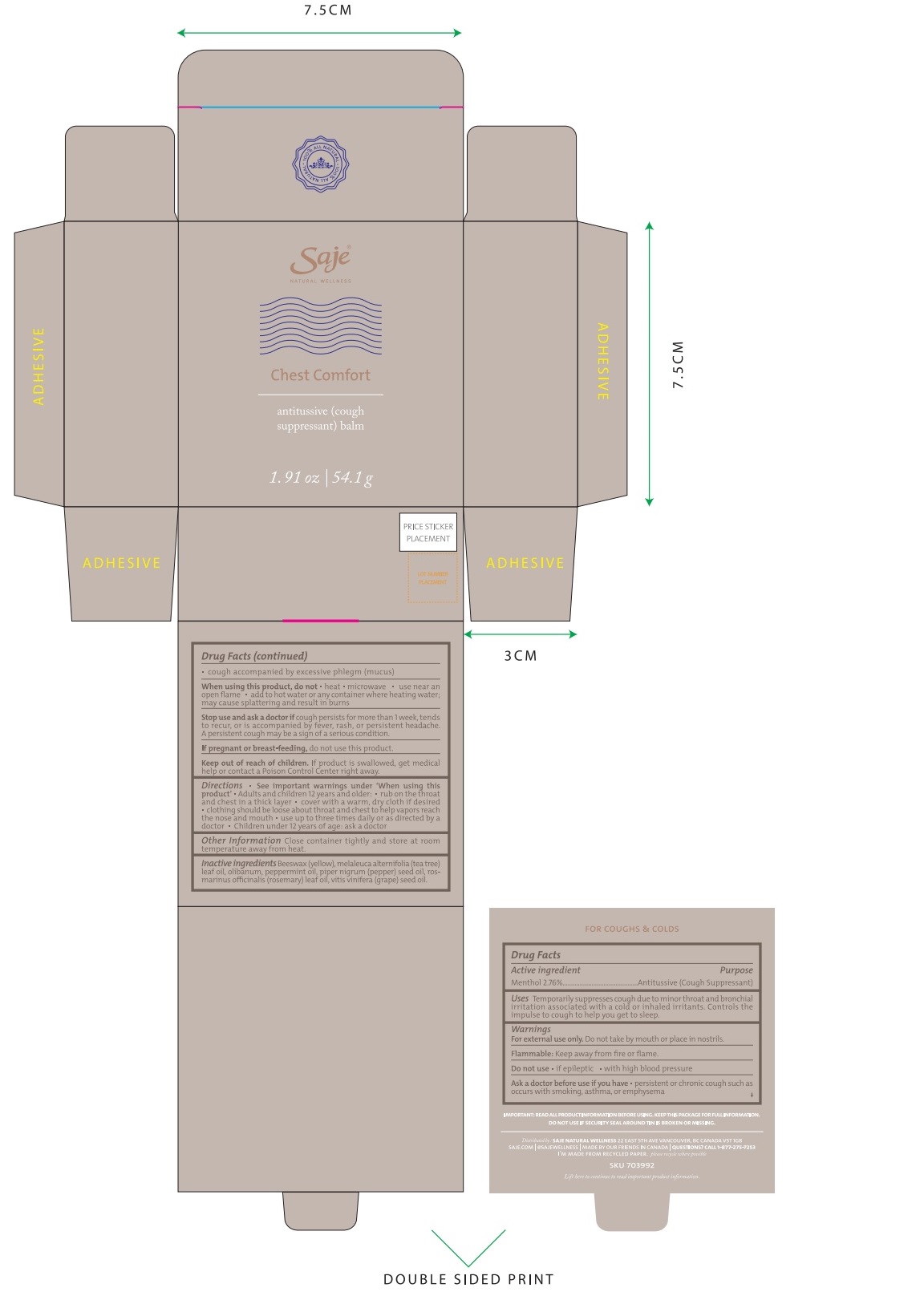 DRUG LABEL: Chest Comfort
NDC: 70983-001 | Form: SALVE
Manufacturer: Saje Natural Business Inc.
Category: otc | Type: HUMAN OTC DRUG LABEL
Date: 20260112

ACTIVE INGREDIENTS: MENTHOL 27.6 mg/1 g
INACTIVE INGREDIENTS: YELLOW WAX; TEA TREE OIL; FRANKINCENSE OIL; PEPPERMINT OIL; BLACK PEPPER OIL; ROSEMARY OIL; GRAPE SEED OIL

Chest Comfort Antitussive (Cough Suppressant) Balm (54.1 g)

ACTIVE INGREDIENT

Menthol 2.76%

Purpose Antitussive (Cough Suppressant)

Uses Temporarily suppresses cough due to minor throat and bronchial irritation associated with a cold or inhaled irritants. Controls the impulse to cough to help you get to sleep.

WARNINGS

For external use only.

Do not take by mouth or place in nostrils

Flammable: Keep away from fire or flame.

DO NOT USE

- if epileptic
- with high blood pressure

Ask a doctor before use if you have

- persistent or chronic cough such as occurs with smoking, asthma, or emphysema
- cough accompanied by excessive phlegm (mucus)

When using this product, do not

- heat
- microwave
- use near an open flame
- add to hot water or any container where heating water. May cause splattering and result in burns.

Stop use and ask a doctor if

cough persists for more than 1 week, tends to recur, or is accompanied by fever, rash, or persistent headache. A persistent cough may be a sign of a serious condition.

If pregnant or breast-feeding,

do not use this product.

Keep out of reach of children. If product is swallowed, get medical help or contact a Poison Control Center right away.

DOSAGE AND ADMINISTRATION

- use up to three times daily or as directed by a doctor.
- Children under 12 years of age: ask a doctor.

STORAGE AND HANDLING

Close container tightly and store at room temperature away from heat.

INACTIVE INGREDIENT

Beeswax (yellow), melaleuca alternifolia (tea tree) leaf oil, olibanum, peppermint oil, piper nigrum (pepper) seed oil, rosmarinus officinalis (rosemary) leaf oil, and vitis vinifera (grape) seed oil.

QUESTIONS

1-877-275-7253

Distributed by: SAJE NATURAL WELLNESS 22 E. 5th Ave. Vancouver, BC Canada V5T 1G8 | saje.com | @sajewellness | Made by our friends in Canada

SKU 703992

Lift here to continue to read important product information

DISPOSAL AND WASTE HANDLING

Please recycle where possible.

IMPORTANT: READ ALL PRODUCT INFORMATION BEFORE USING. KEEP THIS PACKAGE FOR FULL INFORMATION. DO NOT USE IF SECURITY SEAL IS BROKEN OR MISSING.

DESCRIPTION

Chest Comfort, net wt 1.91 oz | 54.1 g, antitussive (cough suppressant) balm

INDICATIONS AND USAGE

- See important warnings under 'When using this product'.
- Adults and children 12 years of age and older: rub on the throat and chest in a thick layer
- cover with a warm, dry cloth if desired
- clothing should be loose about throat and chest to help vapors reach the nose and mouth

PACKAGE LABEL

Saje® Natural Wellness

Chest Comfort

Antitussive (Cough Suppressant) Balm

net wt. 1.91 oz | 54.1 g